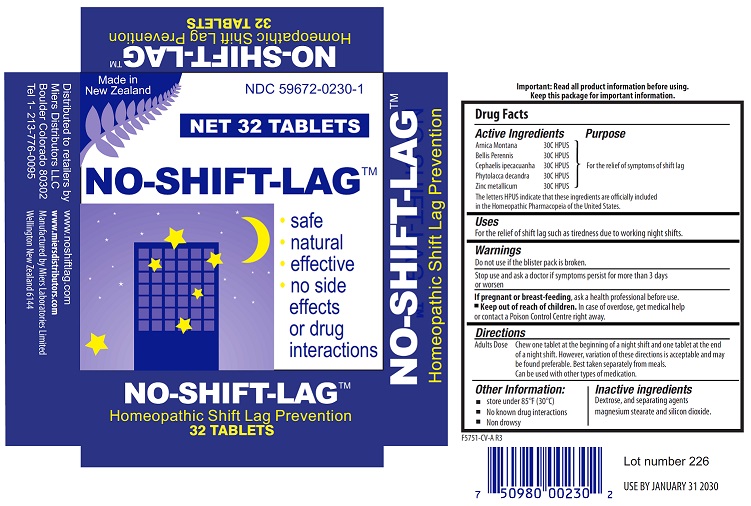 DRUG LABEL: No-Shift-Lag
NDC: 59672-0230 | Form: TABLET
Manufacturer: Miers Laboratories
Category: homeopathic | Type: HUMAN OTC DRUG LABEL
Date: 20251218

ACTIVE INGREDIENTS: ARNICA MONTANA 30 [hp_C]/1 1; BELLIS PERENNIS 30 [hp_C]/1 1; IPECAC 30 [hp_C]/1 1; PHYTOLACCA AMERICANA ROOT 30 [hp_C]/1 1; ZINC 30 [hp_C]/1 1
INACTIVE INGREDIENTS: DEXTROSE, UNSPECIFIED FORM 242 mg/1 1; SILICON DIOXIDE; MAGNESIUM STEARATE

No-Shift-Lag™

Drug Facts

ACTIVE INGREDIENT

Active Ingredients |  | Purpose
Arnica Montana | 30C HPUS | For the relief of symptoms of shift lag
Bellis Perennis | 30C HPUS | For the relief of symptoms of shift lag
Cephaelis ipecacuanha | 30C HPUS | For the relief of symptoms of shift lag
Phytolacca decandra | 30C HPUS | For the relief of symptoms of shift lag
Zinc metallicum | 30C HPUS | For the relief of symptoms of shift lag

Uses

For the relief of shift lag such as tiredness due to working night shifts.

Warnings

Do not use if the blister pack is broken.

Stop use and ask a doctor if symptoms persist for more than 3 days or worsen.

PREGNANCY OR BREAST FEEDING

If pregnant or breast-feeding,ask a health professional before use.

- Keep out of reach of children.

In case of overdose, get medical help or contact a Poison Control Centre right away.

Directions

Adults Dose | Chew one tablet at the beginning of a night shift and one tablet at the end of a night shift. However, variation of these directions is acceptable and may be found preferable. Best taken separately from meals.; Can be used with other types of medication.

Other Information

- store under 85°F (30°C)
- No known drug interactions
- Non drowsy
- Important: Read all product information before using. Keep this package for important information.

Inactive ingredients

Dextrose, and separating agents magnesium stearate and silicon dioxide.

Distributed to retailers by

Miers Distributors LLC

Boulder Colorado 80302

Tel 1- 213-776-0095

www.noshiftlag.com

www.miersdistributors.com

Manufactured by

Miers Laboratories Limited

Wellington New Zealand 6144

PRINCIPAL DISPLAY PANEL - 32 Tablet Blister Pack Carton

Made in New Zealand

NDC 59672-0230-1

NET 32 TABLETS

NO-SHIFT-LAG™

safe natural effective no side effects or drug interactions

Homeopathic Shift Lag Prevention